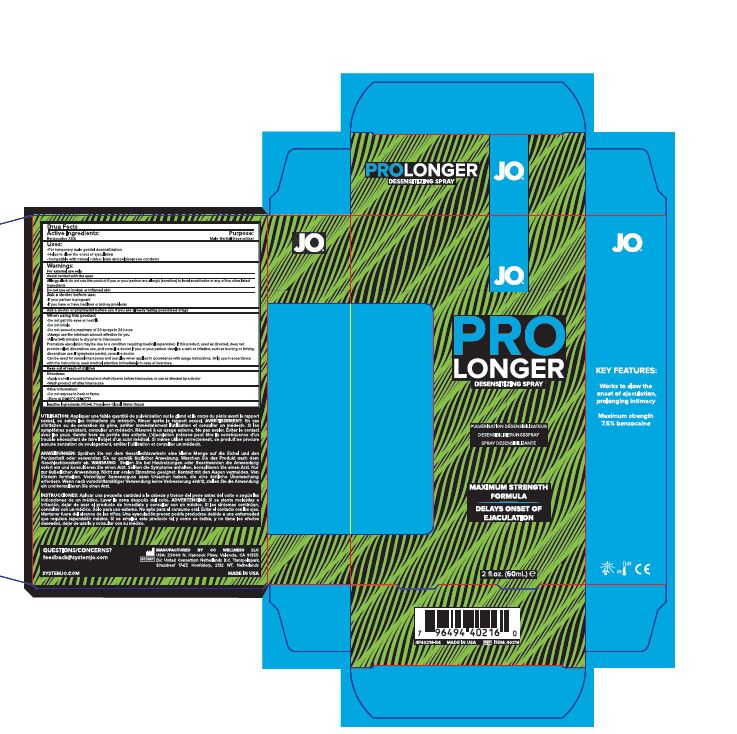 DRUG LABEL: JO Prolonger with Benzocaine
NDC: 71683-004 | Form: SPRAY
Manufacturer: CC Wellness LLC
Category: otc | Type: HUMAN OTC DRUG LABEL
Date: 20250912

ACTIVE INGREDIENTS: BENZOCAINE 7.5 g/100 mL
INACTIVE INGREDIENTS: WATER; PROPYLENE GLYCOL; POLYETHYLENE GLYCOL 400

ACTIVE INGREDIENT

Benzocaine 7.5%

PURPOSE

Male Genital Desensitizer

INDICATIONS AND USAGE

For temporary male genital desensitization

Helps to slow the onset of ejaculation

Compatible with natural rubber latex and polyisoprene condoms

For external use only

Ask a doctor before use

If your partner is pregnant

If you have or have had liver or kidney problems

When using this product

- Do not get into eyes or nostrils
- Do not inhale
- Do not exceed a maximum of 20 sprays in 24 hours
- Always use the minimum amount effective for you
- Allow 5-15 minutes to dry prior to intercourse

Premature ejaculation may be due to a condition requiring medical supervision. If this product, used as directed, does not provide relief, discontinue use, and consult a doctor. If you or your partner develop a rash or irritation, such as burning or itching, discontinue use. If symptoms persist, consult a doctor.

Can be used for sexcual intercourse and sex play when applied in accordance with usage instructions. Only use in accordance with the instructions, seek medical attention immediately in case of overdose.

Directions:

Apply a small amount to head and shaft of penis before intercourse, or use as directed by a doctor.

Wash product off after intercourse.

Other information:

Do not expose to heat or flame.

Store at 20-30°C (68-77°F)

Inactive ingredients:

PEG-8, Propylene Glycol, Water (Aqua)